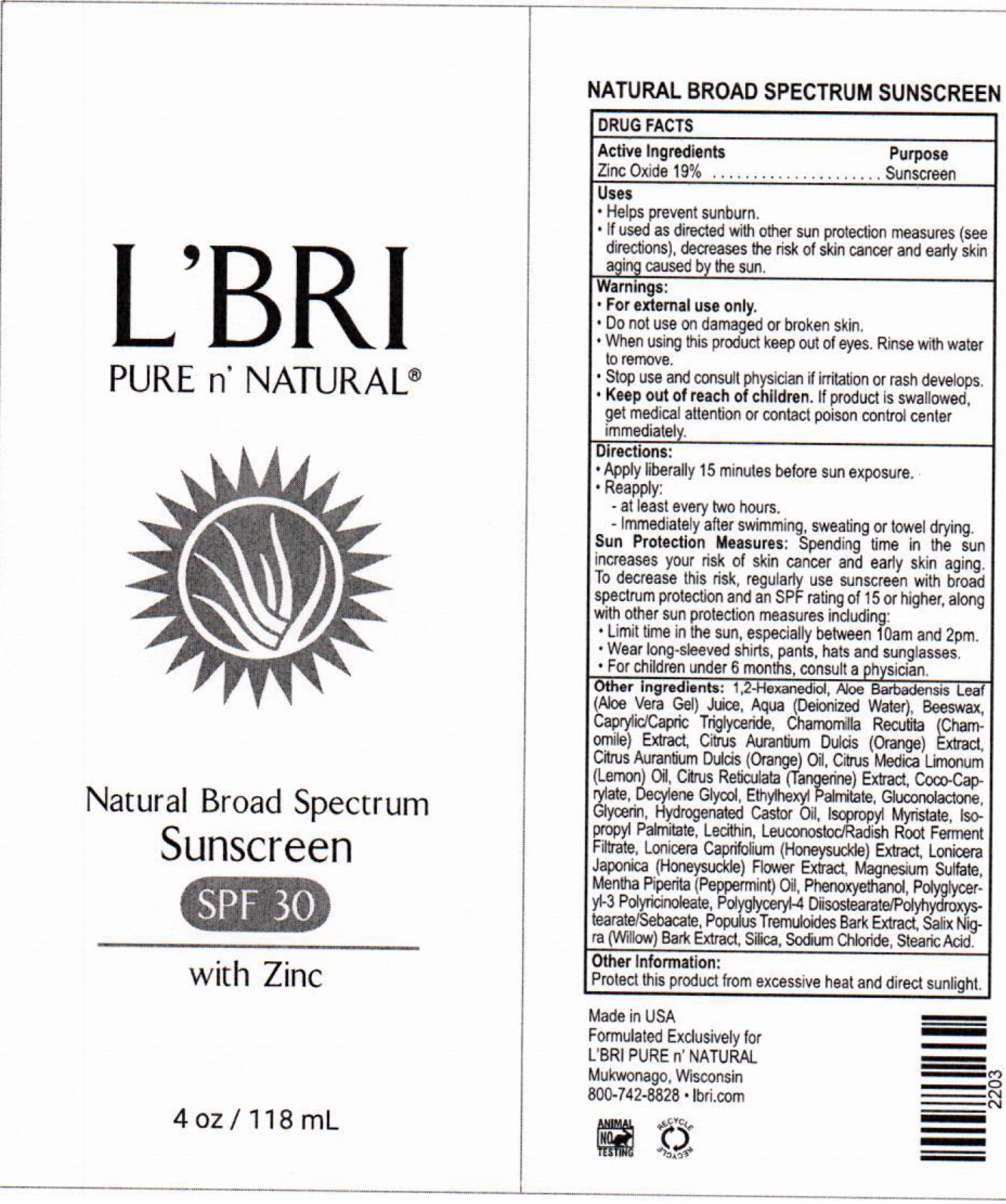 DRUG LABEL: LBri Pure n Natural SPF 30
NDC: 71238-326 | Form: CREAM
Manufacturer: L'BRI HEALTH & BEAUTY
Category: otc | Type: HUMAN OTC DRUG LABEL
Date: 20250403

ACTIVE INGREDIENTS: ZINC OXIDE 190 mg/1 mL
INACTIVE INGREDIENTS: 1,2-HEXANEDIOL; ALOE VERA LEAF; WATER; YELLOW WAX; MEDIUM-CHAIN TRIGLYCERIDES; CHAMOMILE; ORANGE; ORANGE OIL; LEMON; TANGERINE; COCO-CAPRYLATE; DECYLENE GLYCOL; ETHYLHEXYL PALMITATE; GLUCONOLACTONE; GLYCERIN; HYDROGENATED CASTOR OIL; ISOPROPYL MYRISTATE; ISOPROPYL PALMITATE; LEUCONOSTOC/RADISH ROOT FERMENT FILTRATE; LONICERA CAPRIFOLIUM FLOWER; LONICERA JAPONICA FLOWER; MAGNESIUM SULFATE, UNSPECIFIED FORM; PEPPERMINT OIL; PHENOXYETHANOL; POPULUS TREMULOIDES BARK; SALIX NIGRA BARK; SILICON DIOXIDE; SODIUM CHLORIDE; STEARIC ACID

L'Bri Pure n' Natural SPF-30

Active ingredients

Zinc Oxide 19%

Purpose

Sunscreen

Uses

- Helps prevent sunburn.
- If used as directed with other sun protection measures (see directions), decreases the risk of skin cancer and early skin aging caused by the sun.

Warnings

For external use only.

Do not use

on damaged or broken skin.

When using this product

keep out of eyes. Rinse with water to remove.

Stop use and consult physician

if irritation or rash develops.

Keep out of reach of children.

If product is swallowed, get medical attention or contact poison control center immediately.

Directions

- Apply liberally 15-minutes before sun exposure.
- Reapply:

-at least every two-hours.

-Immediately after swimming, sweating or towel drying.

Spending time in the sun increases your risk of skin cancer and ealy skin aging. To decrease this risk, regularly use sunscreen with broad spectrum protection and an SPF rating of 15 or higher, along with other sun protection measures including: SUN PROTECTION MEASURES:

-Limit time in the sun, especially between 10am and 2pm.

-Wear long sleeve shirts, pants, hats and sunglasses.

-For children under 6-months, consult a physician.

Other ingredients

1,2-Hexanediol, Aloe Barbadensis Leaf (Aloe Vera Gel) Juice, Aqua (Deionized Water), Beeswax, Caprylic/Capric Triglyceride, Chamomilla Recutita (Chamomile) Extract, Citrus Aurantium Dulcis (Orange) Extract, Citrus Aurantium Dulcis (Orange) Oil, Citrus Medica Limonum (Lemon) Oil, Citrus Reticulata (Tangerine) Extract, Coco-Caprylate, Decylene Glycol, Ethylhexyl Palmitate, Gluconolactone, Glycerin, Hydrogenated Castor Oil, Isopropyl Myristate, Isopropyl Palmitate, Lecithin, Leuconostoc/Radish Root Ferment Filtrate, Lonicera Caprifolium (Honeysuckle) Extract, Lonicera Japonica (Honeysuckle) Flower Extract, Magnesium Sulfate, Mentha Piperita (Peppermint) Oil, Phenoxyethanol, Polyglyceryl-3 Polyricinoleate, Polyglyceryl-4 Diisostearate/Polyhydroxystearate/Sebacate, Populus Tremuloides Bark Extract, Salix Nigra (Willow) Bark Extract, Silica, Sodium Chloride, Stearic Acid.

Other Information:

Protect the product in this container from excessive heat and direct sunlight.